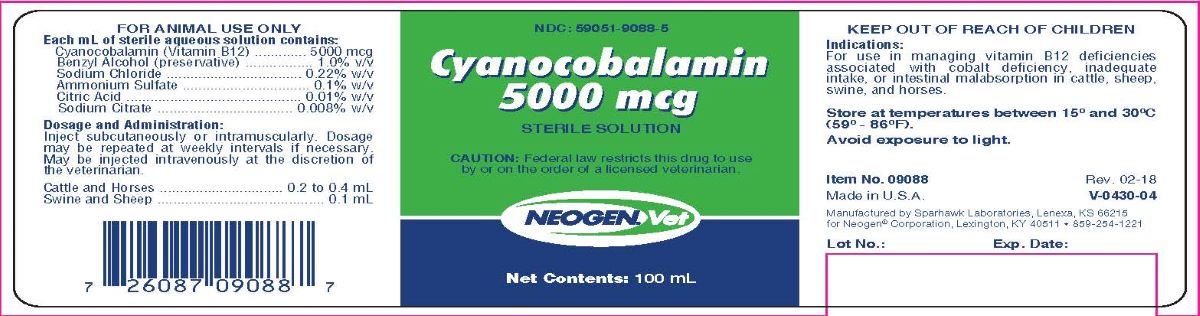 DRUG LABEL: Cyanocobalamin 5000 mcg
NDC: 59051-9088 | Form: INJECTION
Manufacturer: Neogen Corporation - Nandino
Category: animal | Type: PRESCRIPTION ANIMAL DRUG LABEL
Date: 20231219

ACTIVE INGREDIENTS: CYANOCOBALAMIN 5 mg/1 mL
INACTIVE INGREDIENTS: BENZYL ALCOHOL; WATER; SODIUM CHLORIDE; AMMONIUM SULFATE; ANHYDROUS CITRIC ACID; SODIUM CITRATE

Cyanocobalamin
5000 mcg
Sterile Solution

Indications:

For use in managing Vitamin B12 deficiencies associated with cobalt deficiency, inadequate intake, or intestinal malabsorption in
cattle, sheep, swine, and horses.

Each mL of Sterile Aqueous Solution Contains:

Cyanocobalamin (Vitamin B12)..............5000 mcg

Benzyl Alcohol (preservative).................1.0% v/v

Sodium Chloride.................................0.22% w/v

Ammonium Sulfate...............................0.1% w/v

Citric Acid..........................................0.01% w/v

Sodium Citrate..................................0.008% w/v

Dosage and Administration:

Inject subcutaneously or intramuscularly. Dosage may be repeated at weekly intervals if necessary. May be injected intravenously at the discretion of the veterinarian.

Cattle and Horses ............................... 0.2 to 0.4 mL

Swine and Sheep .......................................... 0.1 mL

STORAGE AND HANDLING

Store at temperature between 15° and 30°C (59° - 86°F).

Avoid exposure to light.

Item No. 09088 Rev. 02-18

Made in U.S.A V-0403-04

Manufactured by: Sparhawk Laboratories, Inc., Lenexa, KS 66215

for Neogen® Corporation, Lexington, KY 40511 • 859-254-1221

Principal Display Panel

NDC: 59051-9088-5

Cyanocobalamin
5000 mcg

STERILE SOLUTION

CAUTION: Federal law restricts this drug to use
by or on the order of a licensed veterinarian.

Net Contents: 100 mL

FOR ANIMAL USE ONLY

KEEP OUT OF THE REACH OF CHILDREN